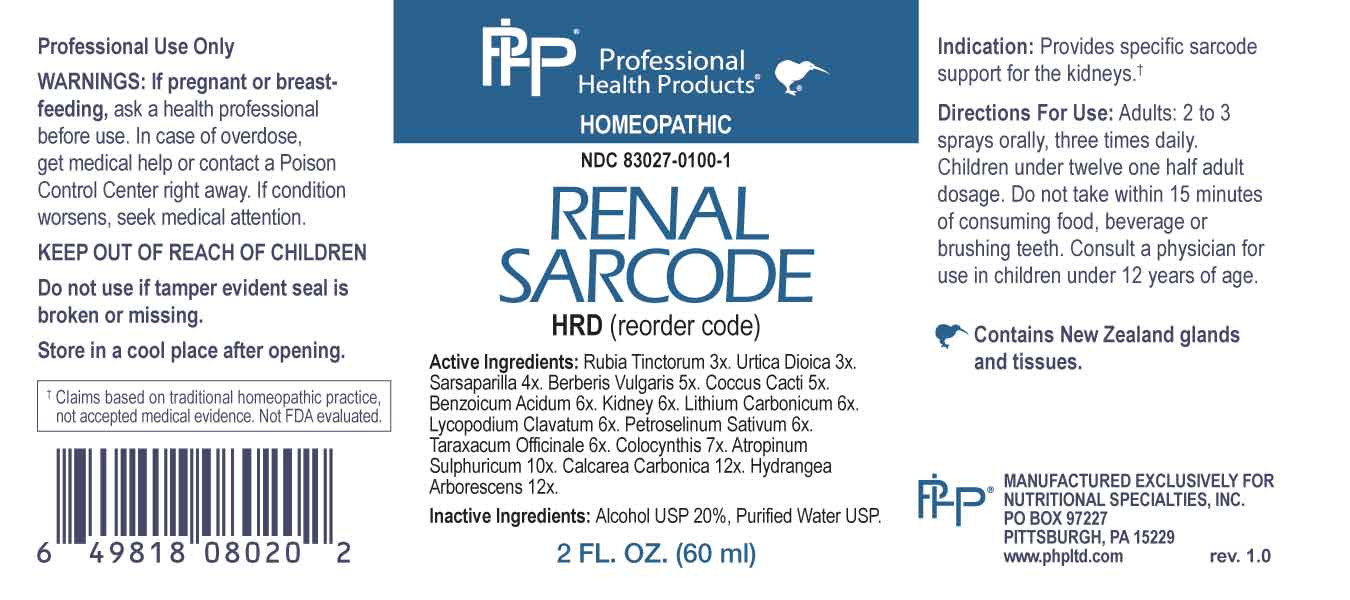 DRUG LABEL: Renal Sarcode
NDC: 83027-0100 | Form: SPRAY
Manufacturer: Nutritional Specialties, Inc.
Category: homeopathic | Type: HUMAN OTC DRUG LABEL
Date: 20230811

ACTIVE INGREDIENTS: RUBIA TINCTORUM ROOT 3 [hp_X]/1 mL; URTICA DIOICA WHOLE 3 [hp_X]/1 mL; SMILAX ORNATA ROOT 4 [hp_X]/1 mL; BERBERIS VULGARIS ROOT BARK 5 [hp_X]/1 mL; PROTORTONIA CACTI 5 [hp_X]/1 mL; BENZOIC ACID 6 [hp_X]/1 mL; BEEF KIDNEY 6 [hp_X]/1 mL; LITHIUM CARBONATE 6 [hp_X]/1 mL; LYCOPODIUM CLAVATUM SPORE 6 [hp_X]/1 mL; PETROSELINUM CRISPUM WHOLE 6 [hp_X]/1 mL; TARAXACUM OFFICINALE 6 [hp_X]/1 mL; CITRULLUS COLOCYNTHIS FRUIT PULP 7 [hp_X]/1 mL; ATROPINE SULFATE 10 [hp_X]/1 mL; OYSTER SHELL CALCIUM CARBONATE, CRUDE 12 [hp_X]/1 mL; HYDRANGEA ARBORESCENS ROOT 12 [hp_X]/1 mL
INACTIVE INGREDIENTS: WATER; ALCOHOL

DRUG FACTS:

ACTIVE INGREDIENTS:

Rubia Tinctorum 3X, Urtica Dioica 3X, Sarsaparilla 4X, Berberis Vulgaris 5X, Coccus Cacti 5X, Benzoicum Acidum 6X, Kidney 6X, Lithium Carbonicum 6X, Lycopodium Clavatum 6X, Petroselinum Sativum 6X, Taraxacum Officinale 6X, Colocynthis 7X, Atropinum Sulphuricum 10X, Calcarea Carbonica 12X, Hydrangea Arborescens 12X.

PURPOSE:

Provides specific sarcode support for the kidneys.†

†Claims based on traditional homeopathic practice, not accepted medical evidence. Not FDA evaluated.

WARNINGS:

Professional Use Only

If pregnant or breast-feeding, ask a health professional before use.

In case of overdose, get medical help or contact a Poison Control Center right away.

If condition worsens, seek medical attention.

KEEP OUT OF REACH OF CHILDREN

Do not use if tamper evident seal is broken or missing.

Store in a cool place after opening

KEEP OUT OF REACH OF CHILDREN:

In case of overdose, get medical help or contact a Poison Control Center right away.

DIRECTIONS:

Adults: 2 to 3 sprays orally, three times daily. Children under twelve one half adult dosage. Do not take within 15 minutes of consuming food, beverage or brushing teeth. Consult a physician for use in children under 12 years of age.

INDICATIONS:

Provides specific sarcode support for the kidneys.†

†Claims based on traditional homeopathic practice, not accepted medical evidence. Not FDA evaluated.

INACTIVE INGREDIENTS:

Alcohol USP 20%, Purified Water USP.

QUESTIONS:

MANUFACTURED EXCLUSIVELY FOR

NUTRITIONAL SPECIALTIES, INC.

PO BOX 97227

PITTSBURG, PA 15229

www.phpltd.com

PACKAGE LABEL DISPLAY:

Professional

Health Products

HOMEOPATHIC

NDC 83027-0100-1

RENAL

SARCODE

2 FL. OZ (60 ml)